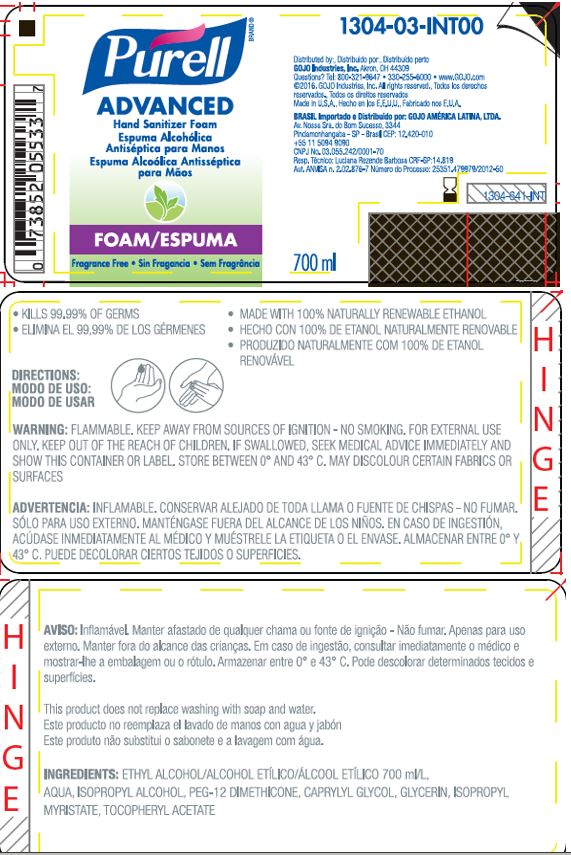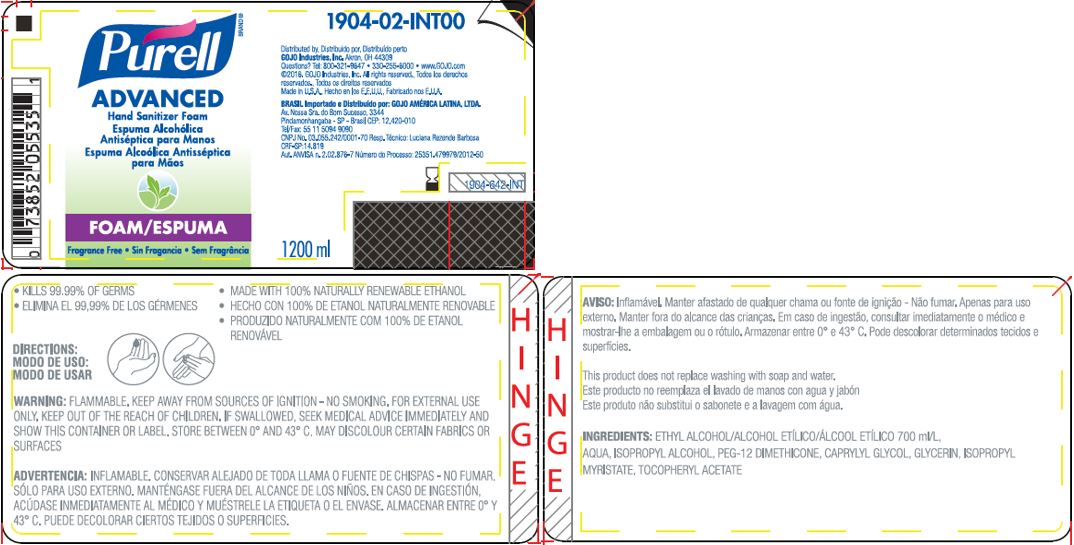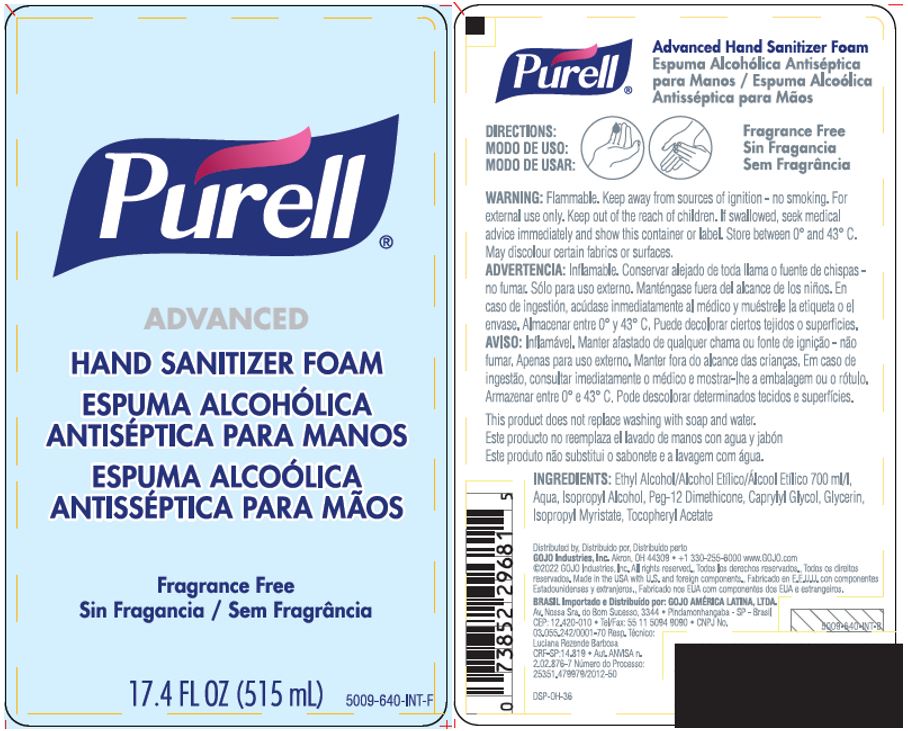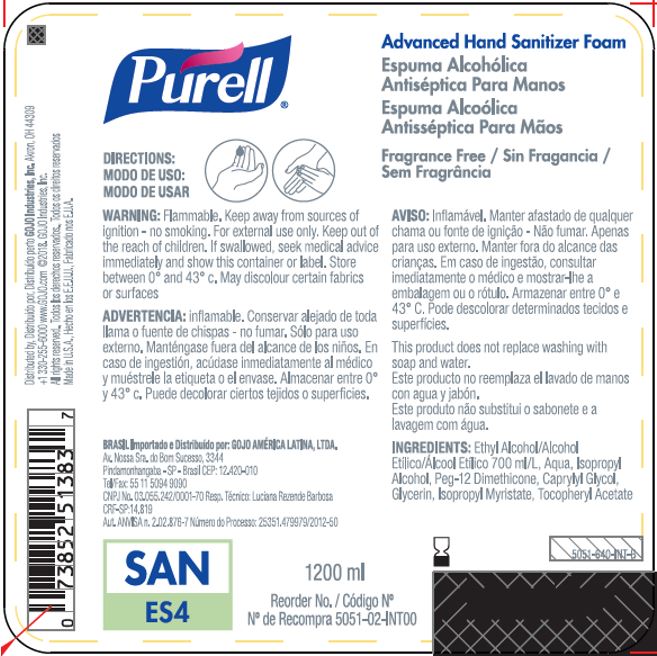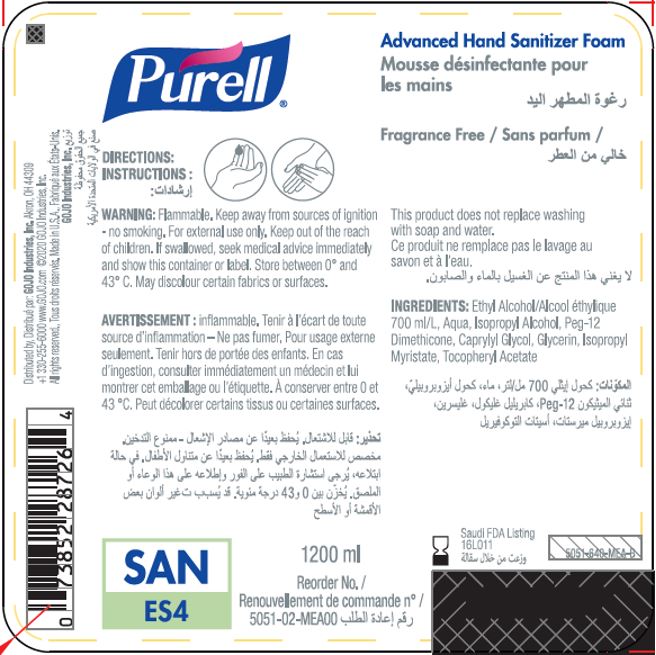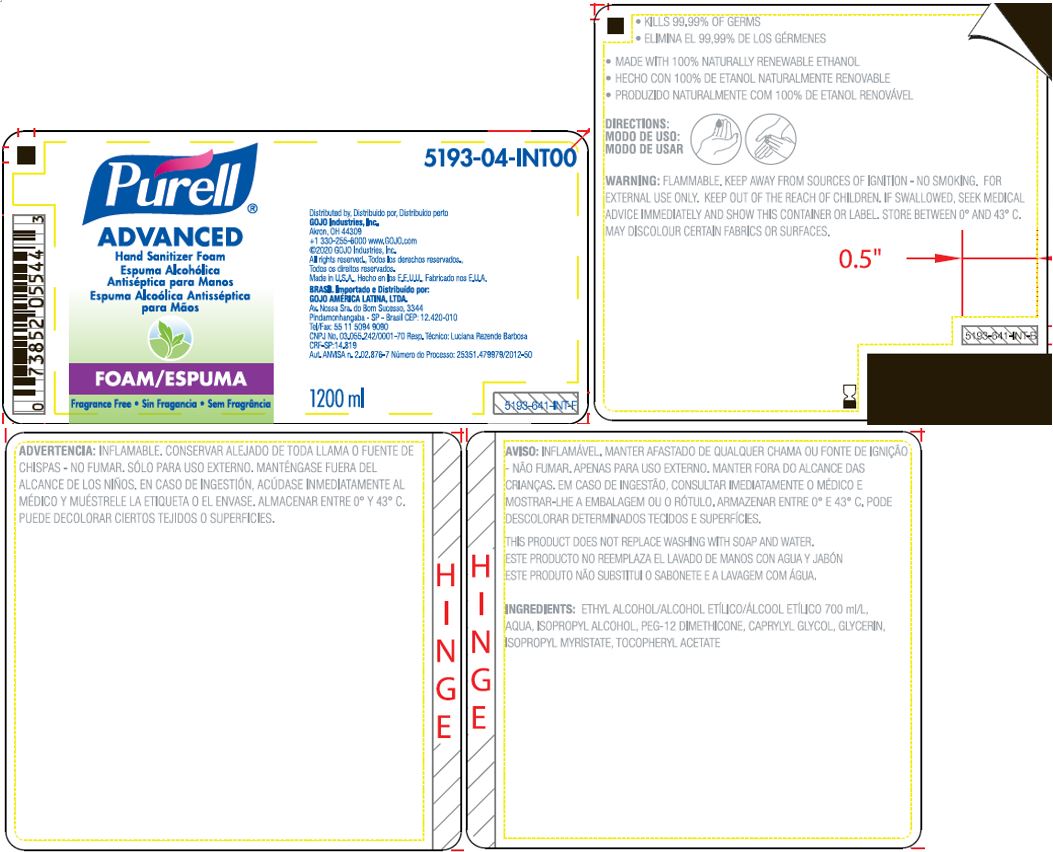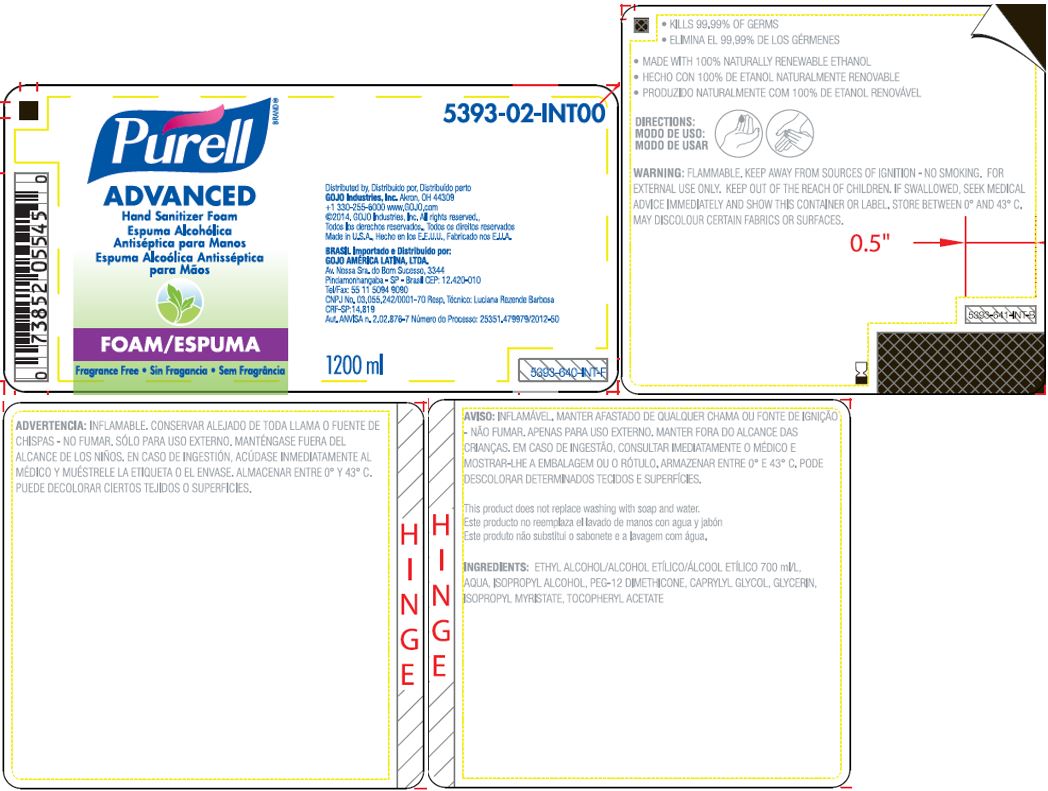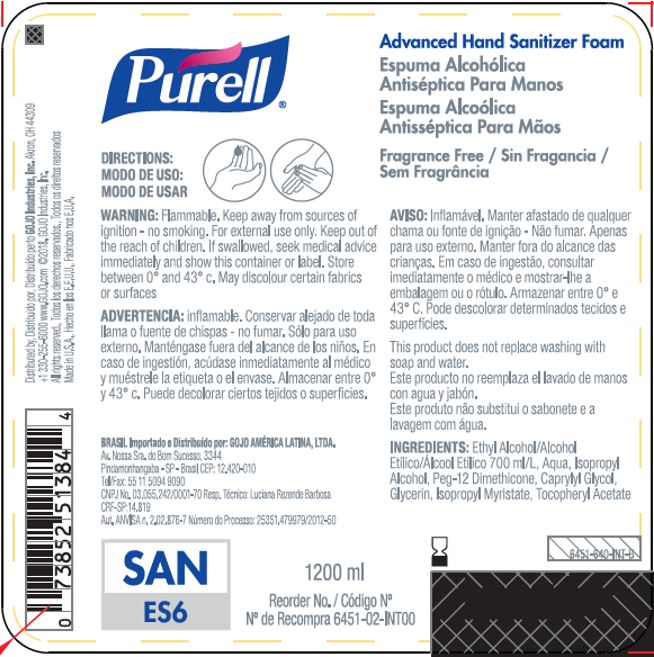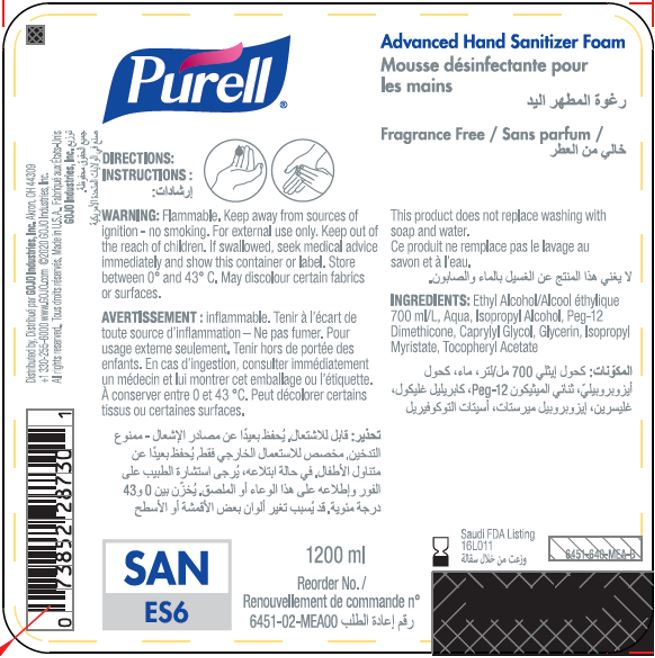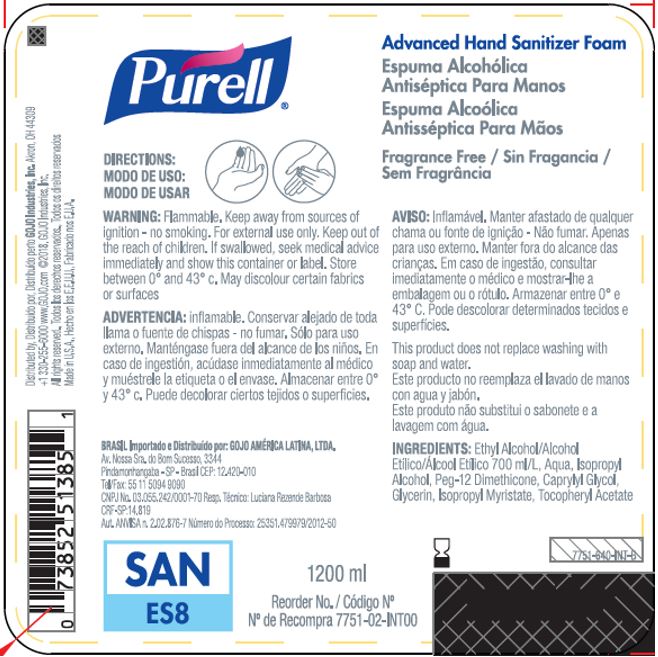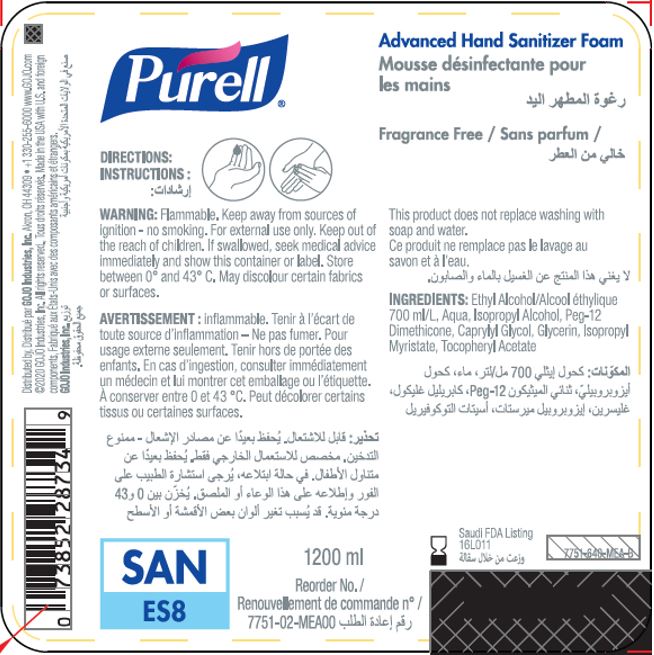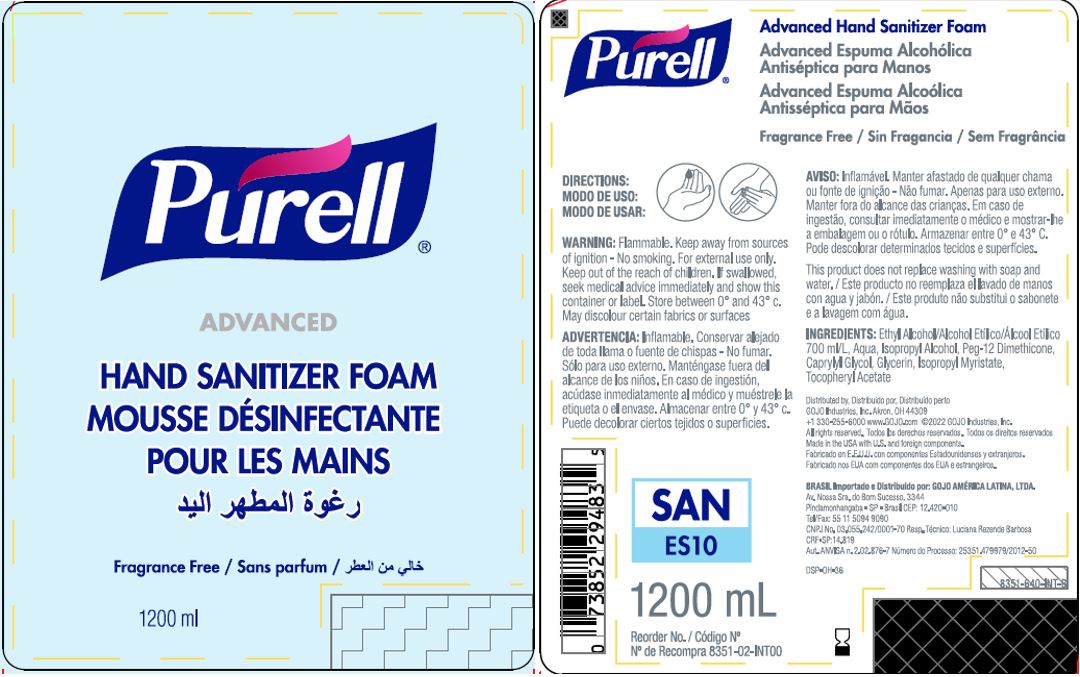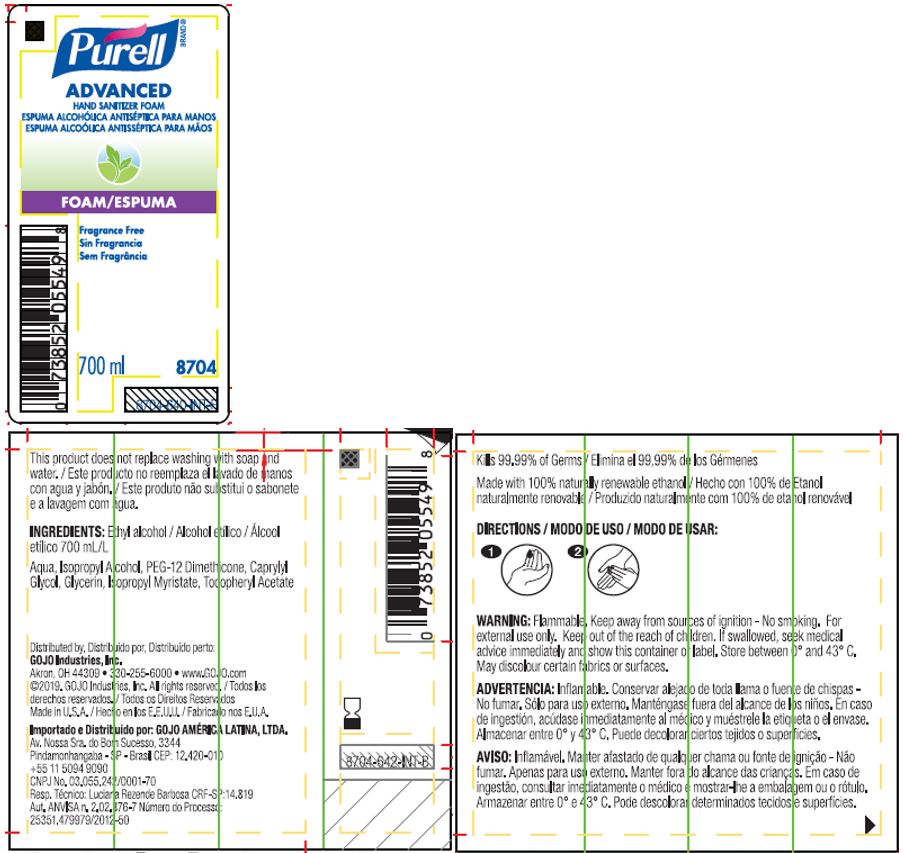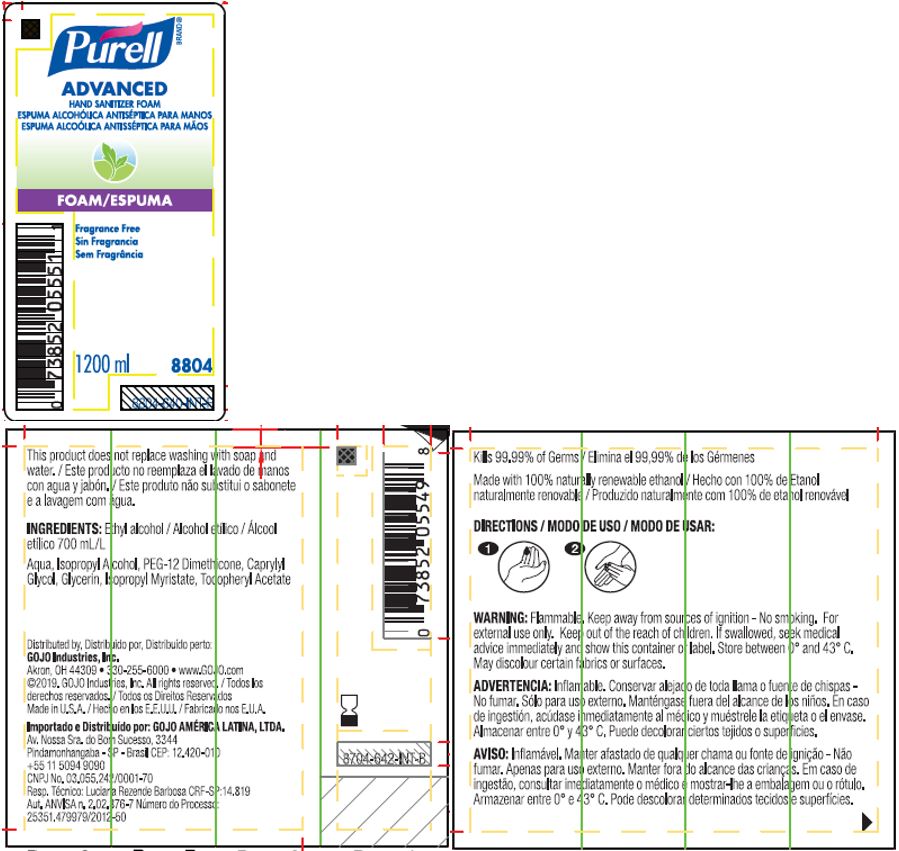 DRUG LABEL: PURELL Advanced Hand Sanitizer Foam
NDC: 21749-030 | Form: LIQUID
Manufacturer: GOJO Industries, Inc.
Category: otc | Type: HUMAN OTC DRUG LABEL
Date: 20241231

ACTIVE INGREDIENTS: ALCOHOL 70 mL/100 mL
INACTIVE INGREDIENTS: WATER; ISOPROPYL ALCOHOL; PEG-12 DIMETHICONE (300 CST); CAPRYLYL GLYCOL; GLYCERIN; ISOPROPYL MYRISTATE; .ALPHA.-TOCOPHEROL ACETATE

PURELL Advanced Hand Sanitizer Foam